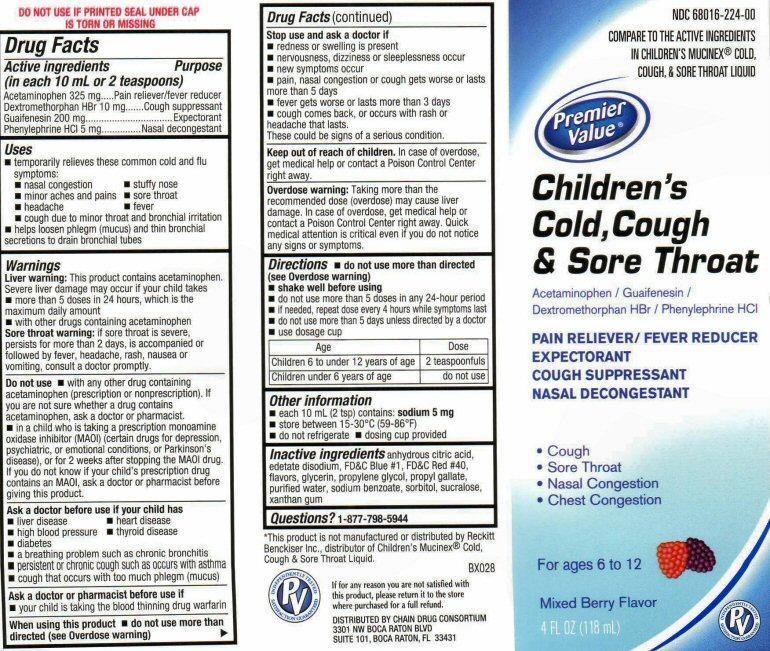 DRUG LABEL: Childrens Cold, Cough and Sore Throat
NDC: 68016-224 | Form: LIQUID
Manufacturer: Chain Drug Consortium, LLC
Category: otc | Type: HUMAN OTC DRUG LABEL
Date: 20130412

ACTIVE INGREDIENTS: ACETAMINOPHEN 325 mg/10 mL; GUAIFENESIN 200 mg/10 mL; DEXTROMETHORPHAN HYDROBROMIDE 10 mg/10 mL; PHENYLEPHRINE HYDROCHLORIDE 5 mg/10 mL
INACTIVE INGREDIENTS: ANHYDROUS CITRIC ACID; EDETATE DISODIUM; FD&C BLUE NO. 1; FD&C RED NO. 40; GLYCERIN; PROPYLENE GLYCOL; PROPYL GALLATE; WATER; SODIUM BENZOATE; SORBITOL; SUCRALOSE; XANTHAN GUM

Active ingredients

Drug Facts
Active ingredients
(in each 10 mL or 2 teaspoons)
Acetaminophen 325 mg
Dextromethorphan HBr 10 mg
Guaifenesin 200 mg
Phenylephrine HCL 5 mg

Purpose

Pain reliever/fever reducer
Cough suppressant
Expectorant
Nasal decongestant

Keep out of reach of children

In case of overdose, get medical help or contact a Poison Control center right away.

Uses

- temporarily relieves these common cold and flu symptoms:
- nasal congestion
- minor aches and pains
- headache
- stuffy nose
- sore throat
- fever
- cough due to minor throat and bronchial irritation
- helps loosen phlegm (mucus) and thin bronchial secretions to drain bronchial tubes

Warnings

Liver warning: This product contains acetaminophen. Sever liver damage may occur if your child if your child takes

- more than 5 doses in 24 hours, which is the maximum daily amount
- with other drugs containing acetaminophen

Sore throat warning: if sore throat is severe, persists for more than 2 days, is accompanied or followed by fever, headache, rash, nausea or vomiting, consult a doctor promptly.

Do not use

- with any other drugs containing acetaminophen (prescription or nonprescription). If you are not sure whether a drug contains acetaminophen, ask a doctor or pharmacist.

- in a child who is taking a prescription monoamine oxidase inhibitor (MAOI) (certain drugs for depression, psychiatric or emotional conditions, or Parkinson’s disease), or for two weeks after stopping the MAOI drug. If you do not know if your child’s prescription drug contains an MAOI, ask a doctor or a pharmacist before taking this product.

Ask a doctor before use if your child has

- liver disease
- high blood pressure
- diabetes
- heart disease
- thyroid disease
- a breathing problem such as chronic bronchitis
- persistent or chronic cough such as occurs with asthma
- cough that occurs with too much phlegm (mucus)

Ask a doctor or pharmacist before use if

- your child is taking the blood thinning drug warfarin

Stop use and ask a doctor if

- redness or swelling is present
- nervousness, dizziness or sleeplessness occur
- new symptoms occur
- pain, nasal congestion or cough gets worse or lasts more that 5 days
- fever gets worse or lasts more than 3 days
- cough comes back, or occurs with rash or headache that lasts.

These could be signs of a serious condition.

Directions

- do not use more than directed (see Overdose warning)
- shake well before using
- do not use more than 5 doses in any 24-hour period
- if needed, repeat dose every 4 hours while symptoms last
- do not use more than 5 days unless directed by a doctor
- use dose cup

Age Dose
Children 6 to under 12 years of age 2 teaspoonfuls
Children under 6 years of age do not use

Other information

- each 10 mL (2 tsp) contains: sodium 5 mg
- store between 15-30 ° C (59-86° F)
- do not refrigerate
- dosing cup provided

Overdose warning

When using this product

- do not use more than directed (see Overdose warning)
- Taking more than the recommended dose (overdose) may cause liver damage. In case of overdose, get medical help or contact a Poison Control Center right away. Quick medical attention is critical even if you do not notice any signs or symptoms.

Inactive ingredients

anhydrous citric acid,edetate disodium, FD and C Blue #1, FD and C Red # 40, flavors, glycerin, propylene glycol, propyl gallate, purified water, sodium benzoate, sorbitol, sucralose, xanthan gum

Questions?

1-877-798-5944

Product Label

NDC 68016-224-00
COMPARE TO THE ACTIVE INGREDIENTS IN CHILDREN’S MUCINEX® COLD, COUGH, and SORE THROAT LIQUID
Premier Value®
Children's Cold, Cough, and Sore Throat
Acetaminophen / Guaifenesin / Dextromethorphan HBr / Phenylephrine HCL
PAIN RELIEVER / FEVER REDUCER
EXPECTORANT
COUGH SUPPRESSANT
NASAL DECONGESTANT
Guaifenesin 100 mg
Dextromethorphan HBr 5 mg
Phenylephrine HCL 2.5 mg
* Cough
* Sore Throat
* Nasal Congestion
* Chest Congestion
For ages 6 to 12
Mixed Berry Flavor
4 FL OZ (118mL)
DO NOT USE IF PRINTED SEAL UNDER CAP IS TORN OR MISSING
INDEPENDENTLY TESTED SATISFACTION GUARANTEED PV
DO NOT USE IF PRINTED SEAL UNDER CAP IS TORN OR MISSING
*This product is not manufactured or distributed by Reckitt Benckiser Inc. distributor of Children’s Mucinex® Cold, Cough and Sore Throat Liquid
If for Any reason you are not satisfied with this product, lease return it to the store where purchased for a full refund.
DISTRIBUTED BY
CHAIN DRUG CONSORTIUM
3301 NW BOCA RATON BLVD
SUITE 101, BOCA RATON, FL 33431
BX028